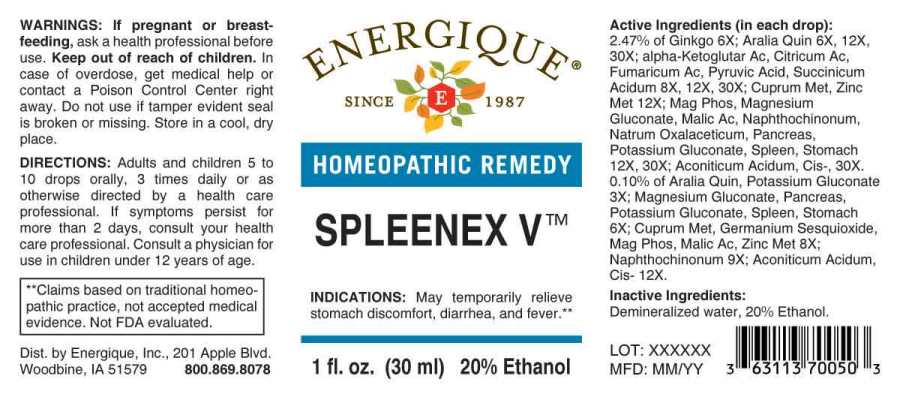 DRUG LABEL: Spleenex
NDC: 44911-0539 | Form: LIQUID
Manufacturer: Energique, Inc.
Category: homeopathic | Type: HUMAN OTC DRUG LABEL
Date: 20241030

ACTIVE INGREDIENTS: AMERICAN GINSENG 3 [hp_X]/1 mL; POTASSIUM GLUCONATE 3 [hp_X]/1 mL; GINKGO 6 [hp_X]/1 mL; MAGNESIUM GLUCONATE 6 [hp_X]/1 mL; SUS SCROFA PANCREAS 6 [hp_X]/1 mL; SUS SCROFA SPLEEN 6 [hp_X]/1 mL; SUS SCROFA STOMACH 6 [hp_X]/1 mL; GERMANIUM SESQUIOXIDE 8 [hp_X]/1 mL; COPPER 8 [hp_X]/1 mL; ZINC 8 [hp_X]/1 mL; OXOGLURIC ACID 8 [hp_X]/1 mL; ANHYDROUS CITRIC ACID 8 [hp_X]/1 mL; FUMARIC ACID 8 [hp_X]/1 mL; MAGNESIUM PHOSPHATE, DIBASIC TRIHYDRATE 8 [hp_X]/1 mL; MALIC ACID 8 [hp_X]/1 mL; PYRUVIC ACID 8 [hp_X]/1 mL; SUCCINIC ACID 8 [hp_X]/1 mL; NAPHTHOQUINE 9 [hp_X]/1 mL; ACONITIC ACID, (Z)- 12 [hp_X]/1 mL; SODIUM DIETHYL OXALACETATE 12 [hp_X]/1 mL
INACTIVE INGREDIENTS: WATER; ALCOHOL

DRUG FACTS:

ACTIVE INGREDIENTS:

(in each drop): 2.47% of Ginkgo Biloba 6X; Aralia Quinquefolia 6X, 12X, 30X; Alpha-Ketoglutaricum Acidum 8X, 12X, 30X, Citricum Acidum 8X, 12X, 30X, Fumaricum Acidum 8X, 12X, 30X, Pyruvic Acid 8X, 12X, 30X, Succinicum Acidum 8X, 12X, 30X; Cuprum Metallicum 12X, Zincum Metallicum 12X; Magnesia Phosphorica 12X, 30X, Magnesium Gluconicum Dihydricum 12X 30X, Malicum Acidum 12X, 30X, Naphthoquinone 12X, 30X, Natrum Oxalaceticum 12X, 30X, Pancreas Suis 12X, 30X, Potassium Gluconate 12X, 30X, Spleen (Suis) 12X, 30X, Stomach (Suis) 12X, 30X; Aconiticum Acidum, Cis 30X. 0.10% of Aralia Quinquefolia 3X, Potassium Gluconate 3X; Magnesium Gluconicum Dihydricum 6X, Pancreas Suis 6X, Potassium Gluconate 6X, Spleen (Suis) 6X, Stomach (Suis) 6X; Cuprum Metallicum 8X, Germanium Sesquioxide 8X, Magnesia Phosphorica 8X, Malicum Acidum 8X, Zincum Metallicum 8X; Naphthoquinone 9X; Aconiticum Acidum, Cis 12X.

INDICATIONS:

May temporarily relieve stomach discomfort, diarrhea, and fever.**

**Claims based on traditional homeopathic practice, not accepted medical evidence. Not FDA evaluated.

WARNINGS:

If pregnant or breast-feeding, ask a health professional before use.

Keep out of reach of children. In case of overdose, get medical help or contact a Poison Control Center right away.

Do not use if tamper evident seal is broken or missing. Store in a cool, dry place.

Keep out of reach of children. In case of overdose, get medical help or contact a Poison Control Center right away.

DIRECTIONS:

Adults and children 5 to 10 drops orally, 3 times daily or as otherwise directed by a health care professional. If symptoms persist for more than 2 days, consult your health care professional. Consult a physician for use in children under 12 years of age.

INDICATIONS:

May temporarily relieve stomach discomfort, diarrhea, and fever.**

**Claims based on traditional homeopathic practice, not accepted medical evidence. Not FDA evaluated.

INACTIVE INGREDIENTS:

Demineralized water, 20% Ethanol.

QUESTIONS:

Dist. by Energique, Inc.

201 Apple Blvd.

Woodbine, IA 51579 800-869-8078

PACKAGE LABEL DISPLAY:

ENERGIQUE

SINCE 1987

HOMEOPATHIC REMEDY

SPLEENEX V

1 fl. oz. (30 ml)